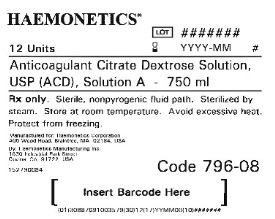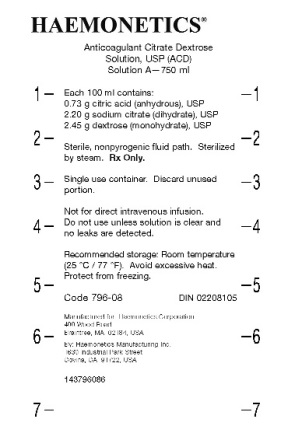 DRUG LABEL: ACD-A
NDC: 53157-796 | Form: SOLUTION
Manufacturer: Haemonetics Manufacturing Inc
Category: prescription | Type: HUMAN PRESCRIPTION DRUG LABEL
Date: 20150209

ACTIVE INGREDIENTS: DEXTROSE MONOHYDRATE 2.45 g/100 mL; SODIUM CITRATE 2.20 g/100 mL; CITRIC ACID MONOHYDRATE 0.73 g/100 mL

Anticoagulant Citrate Dextrose Solution, USP (ACD), Solution A

DESCRIPTION

Re-Order Product Code: 796-08

750 mL volume. Single use container.

Sterile, nonpyrogenic fluid path. Sterilized by steam.

Store at room temperature.

INDICATIONS AND USAGE

For use with automated pheresis equipment only. Use according to equipment manufacturer’s instructions. This unit should be used for pheresis only.

CONTRAINDICATIONS

Not for direct intravenous infusion.

WARNINGS

Avoid excessive heat. Protect from freezing.

PRECAUTIONS

Do not use unless solution is clear and no leaks detected.

General

Rx only. Discard unused portion.

Recommended Storage: Store at room temperature (25°C / 77°F).

HOW SUPPLIED

750 mL volume bag.

Each 100 ml contains:

0.73 g citric acid (anhydrous), USP

2.20 g sodium citrate (dihydrate), USP

2.45 g dextrose (monohydrate), USP

PACKAGE/LABEL PRINCIPAL DISPLAY PANEL

Hot Stamped Bag

Envelope Label

References

HAEMONETICS and THE Blood Management Company are trademarks of Haemonetics Corporation.

Manufactured for:

Haemonetics Corporation

400 Wood Road

Braintree, MA 02184, USA

By: Haemonetics Manufacturing Inc.

1630 Industrial Park Street

Covina, CA 91722, USA